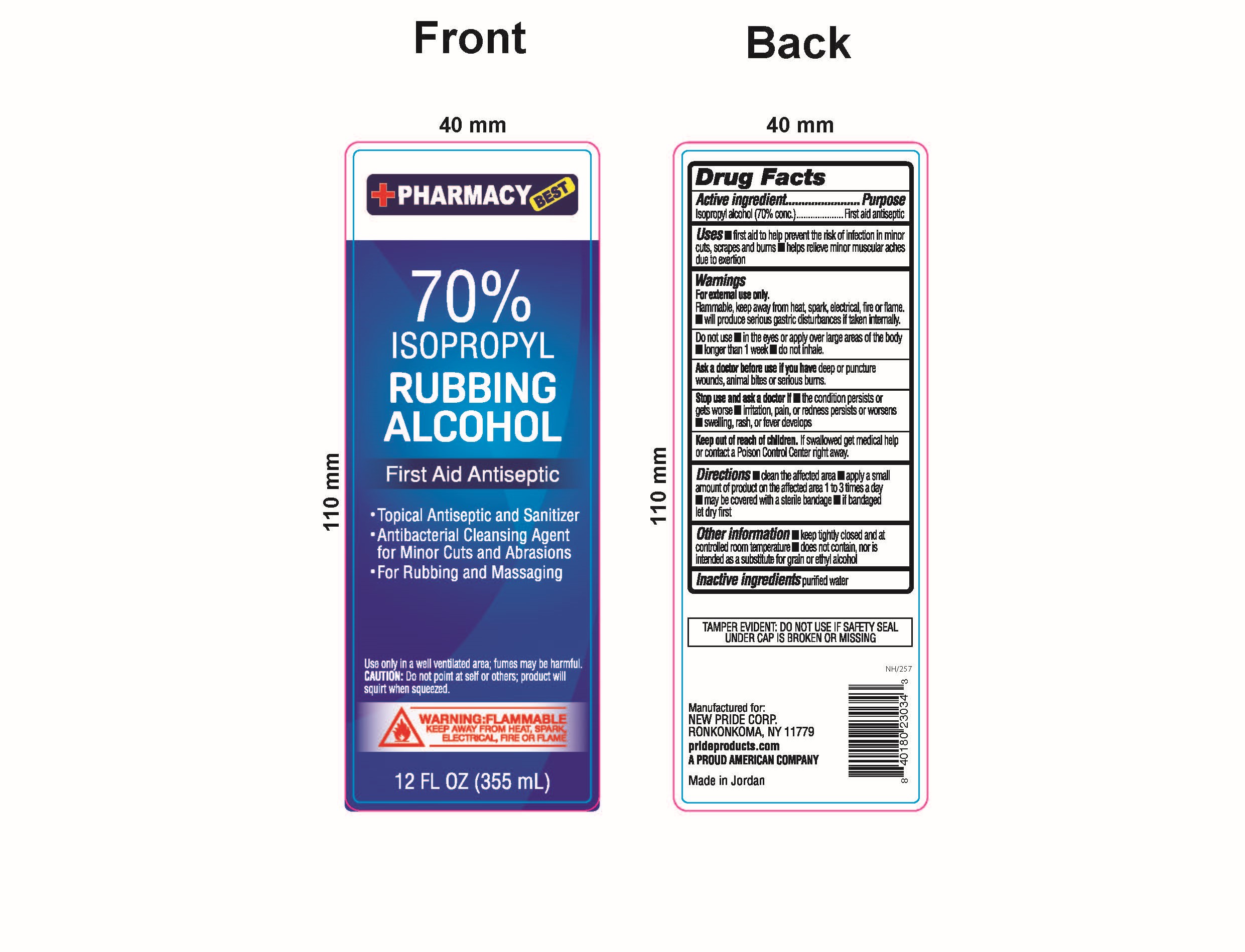 DRUG LABEL: 70% Rubbing Alcohol First Aid Antiseptic
NDC: 58037-704 | Form: LIQUID
Manufacturer: Pride Products Corp.
Category: otc | Type: HUMAN OTC DRUG LABEL
Date: 20240109

ACTIVE INGREDIENTS: ISOPROPYL ALCOHOL 70 mL/100 mL
INACTIVE INGREDIENTS: WATER

Pride Products Corp. 70% Isopropyl Rubbing Alcohol - First Aid Antiseptic

Drug Facts

ACTIVE INGREDIENT

Isopropyl Alcohol (70% conc.)

PURPOSE

First aid antiseptic

USES

- first aid to help prevent the risk of infection in minor cuts, scrapes, and burns
- helps relieve minor muscular aches due to exertion

WARNINGS

For external use only.

Flammable, keep away from heat, spark, electrical, fire or flame.

- will produce serious gastric disturbances if taken internally.

Ask a doctor before use if you have deepor puncture wounds, animal bites or serious burns.

Stop use and ask a doctor if

- the condition persists or gets worse
- irritation, pain, or redness persists or worsens
- swelling, rash, or fever develops

Keep out of reach of children. If swallowed get medical help or contact a Poison Control Center right away.

Directions

- clean the affected area
- apply a small amount of product on the affected area 1 to 3 times a day
- may be covered with a sterile bandage
- if bandaged, let dry first

Other information

- keep tightly closed and at a controlled room temperature
- does not contain, nor is intended as a substitute for grain or ethyl alcohol

INACTIVE INGREDIENT

Purified water.

Do not use

- in the eyes or apply over large areas of the body
- longer than 1 week
- do not inhale

RECENT MAJOR CHANGES

Accidentally selected the wrong heading.

PACKAGE LABEL

PACKAGE LABEL

+PHARMACY BEST

70% ISOPROPYL RUBBING ALCOHOL

First Aid Antiseptic

- Topical Antiseptic and Sanitizer
- Antibacterial Cleansing Agent for Minor Cuts and Abrasions
- For Rubbing and Massaging

Use only in a well ventilated area; fumes may be harmful.

CAUTION: Do not point at self or others; product will squirt when squeezed

WARNING: FLAMMABLE

KEEP AWAY FROM HEAT, SPARK, ELECTRICAL, FIRE OR FLAME

12 FL OZ (355 mL)

TAMPER EVIDENT: DO NOT USE IF SAFETY SEAL UNDER CAP IS BROKEN OR MISSING

Manufactured for:

NEW PRIDE CORP.

RONKONKOMA, NY 11779

prideproducts.com

A PROUD AMERICAN COMPANY

Made in Jordan